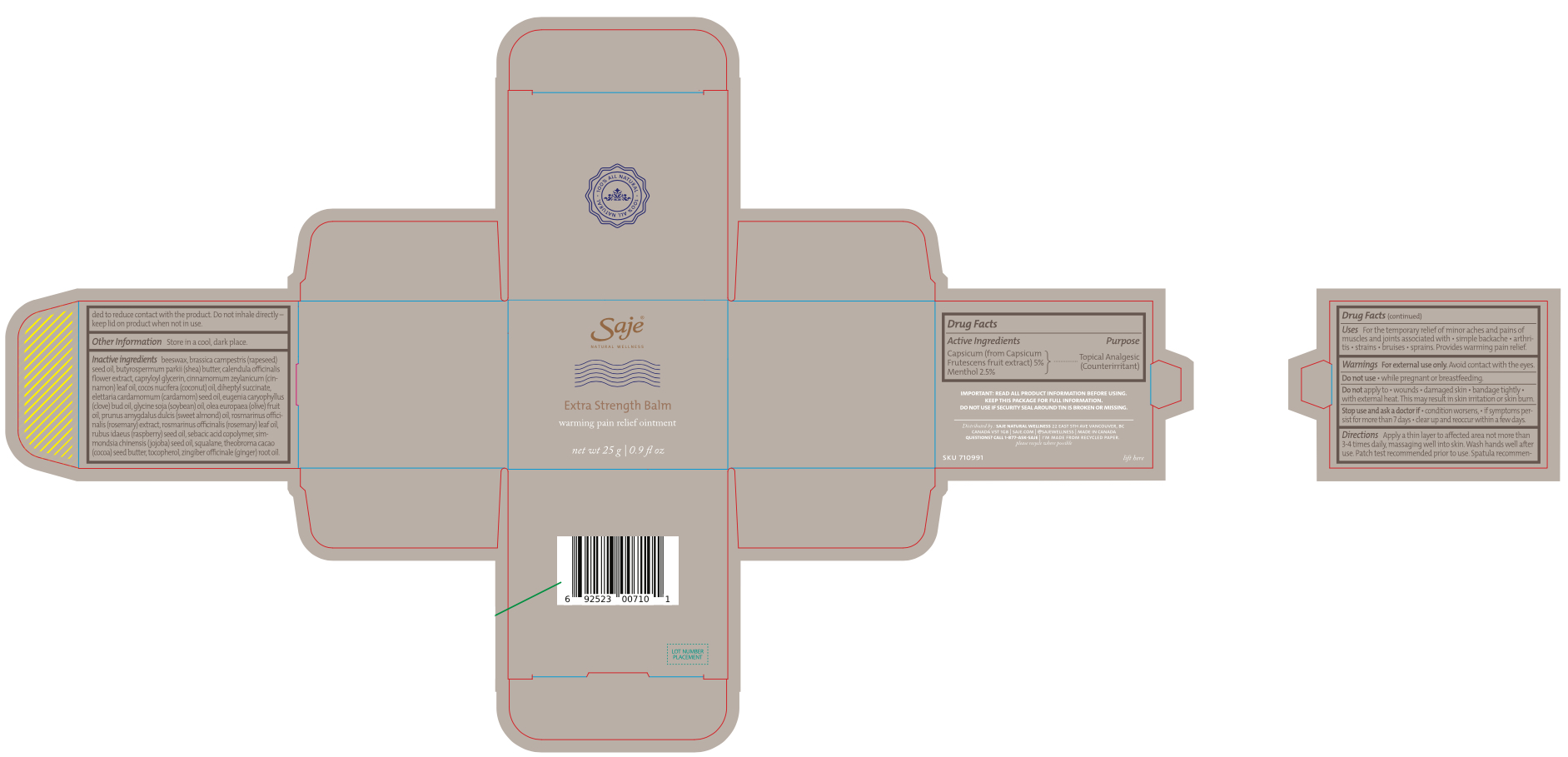 DRUG LABEL: Extra Strength Balm
NDC: 70983-027 | Form: OINTMENT
Manufacturer: Saje Natural Business Inc
Category: otc | Type: HUMAN OTC DRUG LABEL
Date: 20260112

ACTIVE INGREDIENTS: MENTHOL 2258.75 mg/1 g; CAPSICUM 5000 mg/1 g
INACTIVE INGREDIENTS: DIHEPTYL SUCCINATE; JOJOBA OIL; ALMOND OIL; CALENDULA OFFICINALIS FLOWER; SHEA BUTTER; COCOA BUTTER; CAPRYLOYL GLYCERIN/SEBACIC ACID COPOLYMER (2000 MPA.S); SQUALENE; TOCOPHEROL; ROSEMARY; APIS MELLIFERA; OLIVE OIL; CARDAMOM OIL; COCONUT OIL; RASPBERRY SEED OIL; CLOVE OIL; CINNAMON LEAF OIL; SOYBEAN OIL; GINGER OIL; ROSEMARY OIL

Extra Strength Balm

ACTIVE INGREDIENT

Capsicum (from Capsicum Frutescens fruit extract) 5%
Menthol 2.5%

PURPOSE

External analgesic (counterirritant)

INDICATIONS AND USAGE

For the temporary relief of minor aches and pains of muscles and joints associated with • simple backache • arthritis • strains • bruises • sprains. Provides warming pain relief.

WARNINGS

For external use only.

WHEN USING

Avoid contact with the eyes.

Do not use • while pregnant or breastfeeding.

DO NOT USE

Do not apply to • wounds • damaged skin • bandage tightly • with external heat. This may result in skin irritation or skin burn.

Stop use and ask a doctor if • condition worsens, • if symptoms persist for more than 7 days • clear up and reoccur within a few days.

DOSAGE AND ADMINISTRATION

Adults: Apply a thin layer to affected area not more than 3-4 times daily, massaging well into skin. Wash hands well after use. Patch test recommended prior to use. Spatula recommended to reduce contact with the product. Do not inhale directly–keep lid on product when not in use.

STORAGE AND HANDLING

Store in a cool, dark place.

INACTIVE INGREDIENT

Beeswax, butyrospermum parkii (shea) butter, calendula officinalis flower extract, capryloyl glycerin, cinnamomum zeylanicum (cinnamon) leaf oil, cocos nucifera (coconut) oil, diheptyl succinate, elettaria cardamomum (cardamom) seed oil, eugenia caryophyllus (clove) bud oil, glycine soja (soybean) oil, olea europaea (olive) fruit oil, prunus amygdalus dulcis (sweet almond) oil, rosmarinus officinalis (rosemary) extract, rosmarinus officinalis (rosemary) leaf oil, rubus idaeus (raspberry) seed oil, sebacic acid copolymer, simmondsia chinensis (jojoba) seed oil, squalane, theobroma cacao (cocoa) seed butter, tocopherol, zingiber officinale (ginger) root oil

OTHER SAFETY INFORMATION

Important: Read all product information before using. Keep this package for full information.

Do not use if security seal is broken or missing.

distributed by: saje natural wellness 22 east 5th ave vancouver, bc canada v5t 1g8
saje.com | 1-877-ask-saje | @sajewellness
made in Canada

Questions? Call 1-877-ASK-SAJE

I'm made from recycled paper
please recycle where possible

DESCRIPTION

Extra Strength Balm

Warming pain relief ointment

0.9 fl oz (25 g)